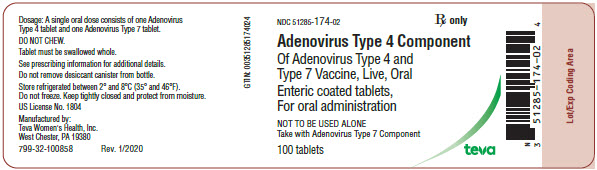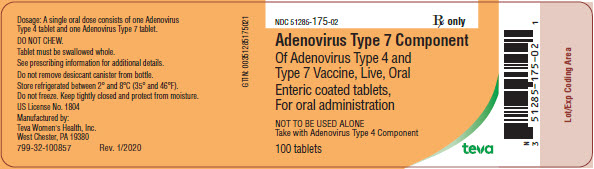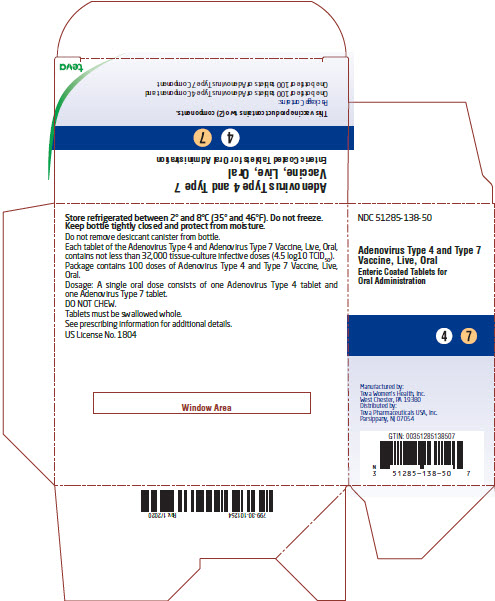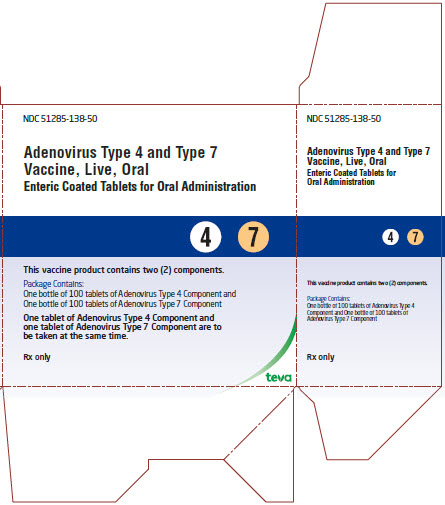 DRUG LABEL: Adenovirus Type 4 and Type 7 Vaccine, Live
NDC: 51285-138 | Form: KIT | Route: ORAL
Manufacturer: Teva Women's Health, Inc.
Category: other | Type: VACCINE LABEL
Date: 20220726

ACTIVE INGREDIENTS: HUMAN ADENOVIRUS E SEROTYPE 4 STRAIN CL-68578 32000 [TCID_50]/1 1; HUMAN ADENOVIRUS B SEROTYPE 7 STRAIN 55142 ANTIGEN 32000 [TCID_50]/1 1
INACTIVE INGREDIENTS: ALBUMIN HUMAN; ANHYDROUS LACTOSE; DEXTROSE; FRUCTOSE; MANNOSE, D-; MAGNESIUM STEARATE; CELLULOSE, MICROCRYSTALLINE; MONOSODIUM GLUTAMATE; POLACRILIN POTASSIUM; POTASSIUM PHOSPHATE, UNSPECIFIED FORM; SUCROSE; CELLACEFATE; CASTOR OIL; ALBUMIN HUMAN; ANHYDROUS LACTOSE; DEXTROSE; FRUCTOSE; MANNOSE, D-; MAGNESIUM STEARATE; CELLULOSE, MICROCRYSTALLINE; MONOSODIUM GLUTAMATE; POLACRILIN POTASSIUM; POTASSIUM PHOSPHATE, UNSPECIFIED FORM; SUCROSE; CELLACEFATE; CASTOR OIL; FD&C YELLOW NO. 6; ALUMINUM OXIDE

HIGHLIGHTS OF PRESCRIBING INFORMATION

These highlights do not include all the information needed to use Adenovirus Type 4 and Type 7 Vaccine, Live, Oral safely and effectively. See full prescribing information for Adenovirus Type 4 and Type 7 Vaccine, Live, Oral.
Adenovirus Type 4 and Type 7 Vaccine, Live, Oral
Enteric Coated Tablets for Oral Administration
Initial U.S. Approval: 2011

1 INDICATIONS AND USAGE

Adenovirus Type 4 and Type 7 Vaccine, Live, Oral is a vaccine indicated for active immunization for the prevention of febrile acute respiratory disease caused by Adenovirus Type 4 and Type 7. Adenovirus Type 4 and Type 7 Vaccine, Live, Oral is approved for use in military populations 17 through 50 years of age. (1)

2 DOSAGE AND ADMINISTRATION

- A single vaccine dose is administered orally as two tablets: one tablet of Adenovirus Type 4 and one tablet of Adenovirus Type 7. (2)
- Each of the two tablets should be swallowed whole. The tablets should not be chewed or crushed to avoid releasing the live adenovirus in the upper respiratory tract.
- Postpone administration in vaccinees with vomiting and/or diarrhea.

3 DOSAGE FORMS AND STRENGTHS

A single oral dose consists of one Adenovirus Type 4 tablet and one Adenovirus Type 7 tablet. (3)

4 CONTRAINDICATIONS

- Pregnancy (4.1, 8.1).
- Severe allergic reaction (e.g., anaphylaxis) to any component of Adenovirus Type 4 and Type 7 Vaccine, Live, Oral is a Contraindication. (4.2, 11)
- Inability to swallow the tablets whole without chewing. (4.3)

5 WARNINGS AND PRECAUTIONS

- Safety and effectiveness have not been evaluated in persons with primary or acquired immunodeficiency states. (5.1)
- Vaccinees and individuals who come in close contact with vaccinees may be exposed to the vaccine viruses shed in the stool for up to 28 days. Proper personal hygiene can minimize this risk. (5.2)
- Vaccinees should exercise caution when in close contact with children less than 7 years of age, immunocompromised individuals and pregnant women during the 28 days following vaccination. (5.2)
- Use effective contraception for 6 weeks after vaccination to avoid pregnancy. (5.3)

6 ADVERSE REACTIONS

The most common (≥ 5%) systemic adverse reactions observed in clinical trials were upper respiratory tract infections, headache, nasal congestion, pharyngolaryngeal pain, cough, arthralgia, nausea, abdominal pain, diarrhea, and vomiting. (6)

To report SUSPECTED ADVERSE REACTIONS, contact Teva Pharmaceuticals at 1-888-483-8279 or VAERS at 1-800-822-7967 or http://vaers.hhs.gov.

8 USE IN SPECIFIC POPULATIONS

Administration during pregnancy is contraindicated (4.1).

FULL PRESCRIBING INFORMATION

1 INDICATIONS AND USAGE

Adenovirus Type 4 and Type 7 Vaccine, Live, Oral is a vaccine indicated for active immunization for the prevention of febrile acute respiratory disease caused by Adenovirus Type 4 and Type 7. Adenovirus Type 4 and Type 7 Vaccine, Live, Oral is approved for use in military populations 17 through 50 years of age.

2 DOSAGE AND ADMINISTRATION

A single vaccine dose is administered orally as two tablets: one tablet of Adenovirus Type 4 and one tablet of Adenovirus Type 7. (2)

The tablets should be swallowed whole, without chewing, to avoid releasing the virus in the upper respiratory tract [See Mechanism of Action (12.1)].

Postpone administration to individuals with vomiting and/or diarrhea because the effectiveness of the vaccine depends upon the multiplication of orally administered live adenovirus within the intestinal tract [See Mechanism of Action (12.1)].

3 DOSAGE FORMS AND STRENGTHS

A single vaccine dose consists of two tablets: one tablet of Adenovirus Type 4 and one tablet of Adenovirus Type 7.

4 CONTRAINDICATIONS

4.1 Pregnancy

Adenovirus Type 4 and Type 7 Vaccine, Live, Oral should not be administered to pregnant females [See Pregnancy (8.1)]. It is not known whether Adenovirus Type 4 and Type 7 Vaccine, Live, Oral can cause fetal harm when administered to a pregnant woman or can affect reproduction capacity. Naturally occurring infection with adenoviruses has been associated with fetal harm. Pregnancy should be avoided for 6 weeks following receipt of vaccine.

4.2 Severe Allergic Reaction

Severe allergic reaction (e.g., anaphylaxis) to any component of Adenovirus Type 4 and Type 7 Vaccine, Live, Oral is a Contraindication [See Description (11)].

4.3 Inability to Swallow

Adenovirus Type 4 and Type 7 Vaccine, Live, Oral should not be administered to individuals incapable of swallowing each entire tablet, whole, without chewing. Chewing a tablet could expose the upper respiratory tract to live adenovirus leading to disease [See Mechanism of Action (12.1)].

5 WARNINGS AND PRECAUTIONS

5.1 Altered Immunocompetence

The safety and effectiveness of Adenovirus Type 4 and Type 7 Vaccine, Live, Oral in immunocompromised individuals has not been evaluated.

5.2 Shedding and Transmission

Adenovirus Type 4 and Type 7 Vaccine, Live, Oral contains live viruses that are shed in the stool and can cause disease if transmitted.

People who come in close contact with those who were vaccinated, including other vaccinees, may be exposed to the virus present in the stool and may develop disease [See Pharmacodynamics (12.2)].

Persons vaccinated with Adenovirus Type 4 and Type 7 Vaccine, Live, Oral should exercise caution when in close contact with children less than 7 years of age and immunocompromised individuals such as those with HIV infection and cancer, or those receiving immunosuppressive therapy during the 28 day period of viral shedding following the vaccination [See Use in Specific Populations (8.3) and Pharmacodynamics (12.2)].

Vaccinees should exercise caution when in close contact with pregnant women during the 28 day period of shedding because fetal harm may result if pregnant women are exposed to adenovirus [See Pregnancy (8.1) and Pharmacodynamics (12.2)].

5.3 Planning for Pregnancy

Use effective contraception for 6 weeks after vaccination to avoid pregnancy [See Pregnancy (8.1)].

5.4 Human Serum Albumin

Adenovirus Type 4 and Type 7 Vaccine, Live, Oral contains albumin, a derivative of human blood. It is present at concentrations of <0.3 mg/tablet. Based on effective donor screening, and product manufacturing processes, it carries an extremely remote risk for transmission of viral diseases. A theoretical risk for transmission of Creutzfeldt-Jakob disease (CJD) also is considered extremely remote. No cases of transmissions of viral diseases or CJD have ever been identified for human albumin.

6 ADVERSE REACTIONS

6.1 Clinical Trials Experience

Because clinical studies are conducted under widely varying conditions, adverse reaction rates observed in the clinical studies of a vaccine cannot be directly compared to the rates in the clinical trials of another vaccine and may not reflect the rates observed in practice.

Multicenter Safety and Efficacy Trial

Safety of Adenovirus Type 4 and Type 7 Vaccine, Live, Oral was evaluated in a multicenter, double-blind, randomized, placebo-controlled study that enrolled 3031 subjects who received vaccine and 1009 subjects who received placebo (lactose tablets). The study was conducted in healthy male (63%) and female (37%) active duty US Army and Navy military recruits during their basic training. The population had a mean age of 21 years, with an age range of 17 to 42 years. Race was 62% Caucasian, 18% African-American, 11% Hispanic, 3% Asian and 6% other. Subjects in both groups were administered other vaccines concomitantly with Adenovirus Type 4 and Type 7 Vaccine, Live, Oral. The specific vaccines that each subject received varied and were dependent on their immunization history. The vaccines that were co-administered included Hepatitis A Vaccine, Inactivated (Merck & Co., Inc.), Hepatitis A Inactivated and Hepatitis B (Recombinant) Vaccine (GlaxoSmithKline Biologicals), Hepatitis B Vaccine (Recombinant) (Merck & Co., Inc.), Human Papillomavirus Quadrivalent (Types 6, 11, 16, 18) Vaccine, Recombinant (Merck & Co., Inc.), Influenza Vaccine, Live, Intranasal (MedImmune, LLC), Influenza Virus Vaccine (Sanofi Pasteur, Inc.), Measles, Mumps, and Rubella Virus Vaccine Live (Merck & Co., Inc.), Meningococcal (Groups A, C, Y and W-135) Polysaccharide, Diphtheria Toxoid Conjugate Vaccine (Sanofi Pasteur, Inc.), Meningococcal Polysaccharide Vaccine (Groups A, C, Y and W-135 Combined) (Sanofi Pasteur, Inc.), Poliovirus Vaccine Inactivated (Sanofi Pasteur, SA), Tetanus Toxoid, Reduced Diphtheria Toxoid and Acellular Pertussis Vaccine, Adsorbed (Sanofi Pasteur, Ltd.), Tetanus Toxoid, Reduced Diphtheria Toxoid and Acellular Pertussis Vaccine, Adsorbed (GlaxoSmithKline Biologicals), Typhoid Vi Polysaccharide Vaccine (Sanofi Pasteur, SA), Varicella Virus Vaccine Live (Merck & Co., Inc.), Yellow Fever Vaccine (Sanofi Pasteur, Inc.).

Serious Adverse Events

No deaths were reported during the multicenter safety and efficacy trial.

Serious adverse events in vaccine recipients included hematuria, gastroenteritis, febrile gastroenteritis, gastritis, pneumonia, and hematochezia.

Fifty-seven serious adverse events (SAEs) were reported during the six month study period with 39 reported between 0 and 56 days following treatment and 18 reported during the 56 to 180 day follow-up period. Thirty-five subjects (1.2%) who received vaccine (25 between 0 and 56 days from the date of vaccination, 10 during the 56 to 180 day follow-up period) and 12 subjects (1.2%) who received placebo (9 between 0 and 56 days from the date of treatment, 3 during the 56 to 180 day follow-up period) experienced at least one SAE. The SAEs occurring between Day 0 and Day 56 post-vaccination in the vaccine group, possibly associated with the receipt of the vaccine product as determined by the investigator, were as follows: one subject with hematuria and gastroenteritis (at 9 days post vaccination), one subject with febrile gastroenteritis (at 4 days post vaccination, one subject with gastritis (at 23 days post vaccination), and one subject with pneumonia (at 23 days post vaccination); one SAE (hematochezia) in the vaccine group occurred during the 56 to 180 day follow-up period and was determined to be possibly related to the vaccine product. A placebo recipient developed febrile acute respiratory disease where adenovirus Type 4 vaccine strain was detected from posterior pharyngeal and tonsillar swabbing and characterized by serotyping and polymerase chain reaction analysis [See Warnings and Precautions: Shedding and Transmission (5.2)].

Overall, the percentage of subjects who experienced at least one adverse event during the 56 day study period was 91.2% in the Adenovirus Type 4 and Type 7 Vaccine, Live, Oral group compared to 93.9% in the placebo group. No subject in either treatment arm discontinued the study due to an adverse event. Adverse reactions were captured on a 2-Week Daily Diary (for a minimum of the first 780 subjects) or a 1-Week Daily Diary (for all remaining subjects) and were also reported at each study visit up to Day 56 after vaccination. Any reported AEs for Days 0-14 for the safety cohort and for Days 0-7 for the remaining subjects were defined as "solicited" because they were almost exclusively recorded directly by the subject from a pre-defined diary checklist. Although pyrexia was defined as “solicited,” it was not on the pre-defined diary checklist. Any AEs reported spontaneously as part of the regular study visit or during a spontaneous visit to the clinic, for Days 15-56 for the safety cohort and Days 8-56 for the remaining subjects were designated as "non-solicited."

Solicited Adverse Reactions

The following solicited adverse reactions were collected through daily diaries: stuffy nose, cough, sore throat, stomach pain, headache, diarrhea, nausea, and joint pain (within 14 days post enrollment for subjects in the initial safety cohort (n=878) and within 7 days post enrollment all subjects (n= 4040) for the rest of safety population). Those solicited adverse reactions reported by ≥ 5 % of subjects in either the vaccine or placebo treatment groups are presented in Table 1.

Table 1: Solicited Adverse Reactions, Days 0-7 for All Subjects and Days 8-14 for the Safety Cohort, Reported by ≥ 5% of Subjects in the Multicenter Safety and Efficacy Trial
Adverse; Reaction* | Adenovirus Type 4 and Type 7 Vaccine, Live, Oral |  |  |  | Placebo
Adverse; Reaction* | 0-7 Days; N = 3031 |  | 8-14 Days; N = 660 |  | 0-7 Days; N = 1009 |  | 8-14 Days; N = 218
Adverse; Reaction*
Adverse; Reaction* | n | % | n | % | n | % | n | %
Headache | 894 | 29.5 | 38 | 6.5 | 310 | 30.7 | 11 | 5.6
Nasal Congestion (Stuffy Nose) | 463 | 15.3 | 49 | 8.4 | 141 | 14.0 | 12 | 6.2
Pharyngolaryngeal Pain (Sore Throat) | 391 | 12.9 | 72 | 12.3 | 124 | 12.3 | 24 | 12.3
Cough | 375 | 12.4 | 59 | 10.1 | 130 | 12.9 | 14 | 7.2
Nausea | 412 | 13.6 | 29 | 5.0 | 137 | 13.6 | 11 | 5.6
Diarrhea | 310 | 10.2 | 18 | 3.1 | 84 | 8.3 | 10 | 5.1

*MedDRA Preferred Term

Pyrexia (temp ≥ 100.5°F) within 7 days, was reported to occur in 1.4% (42/3030) of vaccine recipients and 0.5% (5/961) of placebo recipients who were not diagnosed with ARD. During the 8-14 days post vaccination, rates of pyrexia were 0.6% (4/659) and 1.1% (2/170) in vaccine and placebo recipients, respectively.

Non-Solicited Adverse Reactions

Non-solicited adverse reactions that occurred Days 15-56 in the safety cohort and Days 8-56 for all remaining subjects, reported by ≥ 5 % of subjects in either the vaccine or placebo treatment groups, are presented in Table 2.

Table 2: Non-solicited Adverse Reactions, Days 15-56 for the Safety Cohort and Days 8-56 for all Remaining Subjects, Reported by ≥ 5% of Subjects in the Multicenter Safety and Efficacy Trial
Adverse Reaction* | Adenovirus Type 4 and Type 7 Vaccine, Live, Oral N=3031 |  | Placebo N=1009
 | N | % | N | %
Upper Respiratory Tract Infection | 1135 | 37.5 | 397 | 39.4
Arthralgia | 524 | 17.3 | 180 | 17.8
Abdominal Pain Upper | 443 | 14.6 | 157 | 15.6
Headache | 330 | 10.9 | 148 | 14.7
Cough | 257 | 8.5 | 91 | 9.0
Pharyngolaryngeal Pain | 253 | 8.4 | 73 | 7.2
Nasal Congestion | 229 | 7.6 | 73 | 7.2
Vomiting | 160 | 5.3 | 55 | 5.5
Chills | 77 | 2.5 | 51 | 5.1

*MedDRA Preferred Term

Less common (less than 5%) adverse reactions reported in the clinical trial in military recruits receiving Adenovirus Type 4 and Type 7 Vaccine, Live, Oral, versus placebo, respectively included rhinorrhea (128 [4.22%] vs. 25 [2.48%]), pain in extremity (130 [4.29%] vs. 37 [3.67%]), and pyrexia (fever greater than or equal to 100.5 °F) (126 [4.16%] vs. 49 [4.86%]).

Safety and Immunogenicity Trial

Five SAEs were reported among the 58 subjects in the safety and immunogenicity trial. Two SAEs occurred among the vaccine recipients: one case of pneumonia reported on Day 33 of the follow-up period, and a report of appendicitis occurring on Day 118 of follow-up period. Three SAEs were reported among placebo recipients: one case of pneumonia on Day 10 and one case of upper respiratory infection reported on Day 14, and a right thigh abscess reported at Day 91.

6.2 Postmarketing Experience

The following adverse reactions have been identified during post approval use of Adenovirus Type 4 and Type 7 Vaccine, Live, Oral. Because these reactions are reported voluntarily from a population of uncertain size, it is not always possible to reliably estimate their frequency or establish a causal relationship to vaccine exposure.

Immune System Disorders: Hypersensitivity reactions (including anaphylaxis)

Nervous System Disorders: Guillain-Barré syndrome

7 DRUG INTERACTIONS

7.1 Concomitant Vaccine Administration

In clinical studies Adenovirus Type 4 and Type 7 Vaccine, Live, Oral was administered concurrently with other vaccines [See Adverse Reactions (6.1)]. Data were not available to assess whether Adenovirus Type 4 and Type 7 Vaccine, Live, Oral interferes with the immune response to the other vaccines.

7.2 Immunosuppressive Therapies

There are no data regarding the use of Adenovirus Type 4 and Type 7 Vaccine, Live, Oral concomitantly with immunosuppressive therapies, e.g., irradiation, antimetabolites, alkylating agents, cytotoxic drugs, and corticosteroids (used in greater than physiologic doses) [See Warnings and Precautions: Altered Immunocompetence (5.1)].

8 USE IN SPECIFIC POPULATIONS

8.1 Pregnancy

Risk Summary

Do not administer Adenovirus Type 4 and Type 7 Vaccine, Live, Oral to pregnant females [See Contraindications (4.1)]. It is not known whether Adenovirus Type 4 and Type 7 Vaccine, Live, Oral can cause fetal harm when administered to a pregnant woman. Naturally occurring infection with adenoviruses has been associated with fetal harm.

Pregnancy should be avoided for 6 weeks following receipt of vaccine.

In the US general population, the estimated background risk of major birth defects and miscarriage in clinically recognized pregnancies is 2% to 4% and 15% to 20%, respectively.

Clinical Considerations

Labor and Delivery

There is no information regarding the effect of Adenovirus Type 4 and Type 7 Vaccine, Live, Oral on labor and delivery. Fecal shedding during delivery may result in vaccine virus transmission to the newborn infant.

Data

Human Data

Five pregnancies were reported among women enrolled in the multicenter safety and efficacy trial of Adenovirus Type 4 and Type 7 Vaccine, Live, Oral. Four of the subjects (3 vaccine recipients and 1 placebo recipient) were estimated to have conceived 2 to 13 days prior to vaccination. One subject (vaccine recipient) conceived approximately 21 weeks after vaccination. The deliveries to all five of the subjects were of healthy infants at estimated gestational ages between 36 and 40 weeks.

8.2 Lactation

Risk Summary

There are no data on the presence of Adenovirus Type 4 and Type 7 Vaccine, Live, Oral in human milk, effects on milk production, or on the breastfed infant.

The developmental and health benefits of breastfeeding should be considered along with the mother’s clinical need for Adenovirus Type 4 and Type 7 Vaccine, Live, Oral and any potential adverse effects on the breastfed infant from Adenovirus Type 4 and Type 7 Vaccine, Live, Oral or from the underlying maternal condition. For preventive vaccines, the underlying maternal condition is susceptibility to disease prevented by the vaccine.

8.3 Females and Males of Reproductive Potential

Pregnancy Testing

Adenovirus Type 4 and Type 7 Vaccine, Live, Oral is contraindicated for use in pregnant women [See Pregnancy (4.1)]. Females of reproductive potential should have a pregnancy test prior to treatment with Adenovirus Type 4 and Type 7 Vaccine, Live, Oral.

Contraception

Advise females of reproductive potential to use effective contraception during treatment with Adenovirus Type 4 and Type 7 Vaccine, Live, Oral and for 6 weeks following receipt of vaccine.

8.4 Pediatric Use

The safety and effectiveness of Adenovirus Type 4 and Type 7 Vaccine, Live, Oral has not been evaluated in the age groups from birth through age 16.

8.5 Geriatric Use

Clinical studies of Adenovirus Type 4 and Type 7 Vaccine, Live, Oral did not include subjects aged 65 and over to determine whether they respond differently from younger subjects. There are no data to support use of this vaccine in geriatric (person ≥ 65 years) populations.

11 DESCRIPTION

Adenovirus Type 4 and Type 7 Vaccine, Live, Oral contains viable, selected strains of human adenovirus Type 4 and human adenovirus Type 7 prepared in human-diploid fibroblast cell cultures (strain WI-38). The virus strains have not been attenuated. The cells are grown and the virus growth maintained in Dulbecco’s Modified Eagle’s Medium, fetal bovine serum, and sodium bicarbonate. The virus is harvested, freed of particulate cellular material by filtration, formulated and dried by lyophilization. The dried virus material includes monosodium glutamate, sucrose, D-mannose, D-fructose, dextrose, human serum albumin, potassium phosphate, and plasdone C.

The final vaccine is composed of two tablets (one tablet of Adenovirus Type 4 and one tablet of Adenovirus Type 7) designed to pass intact through the stomach and release the live virus in the intestine. Each enteric-coated tablet contains an inner core tablet containing anhydrous lactose, microcrystalline cellulose, polacrilin potassium, magnesium stearate, and live adenovirus, either Type 4 or Type 7, at a potency of no fewer than 32,000 tissue-culture infective doses (4.5 log10 TCID50) per tablet. The outer tablet layer contains microcrystalline cellulose, magnesium stearate, and anhydrous lactose, with an enteric coating consisting of cellulose acetate phthalate, alcohol, acetone, and castor oil. The Type 7 tablet also contains FD&C Yellow #6 aluminum lake dye.

12 CLINICAL PHARMACOLOGY

12.1 Mechanism of Action

Adenovirus Type 4 and Type 7 Vaccine, Live, Oral is a live oral vaccine that replicates in the intestinal tract and induces immunity in persons with low or no pre-existing neutralizing antibodies.

12.2 Pharmacodynamics

Vaccine Virus Shedding

Fecal shedding of Adenovirus Type 4 and Type 7 Vaccine, Live, Oral strain viruses was evaluated in a safety and immunogenicity study of 58 subjects (30 vaccine recipients and 28 placebo recipients) [See Clinical Studies (14)]. Stool or rectal swabs and throat swabs were collected on Day 0, 7, 14, 21, 28 and 56. Vaccine virus strains were shed in the stool as early as day 7 following vaccination. Eight of 30 vaccine recipients (27%) tested positive at least once for Adenovirus Type 4 fecal shedding; 18 of 30 vaccine recipients (60%) tested positive for Adenovirus Type 7 fecal shedding. No adenovirus shedding was detectable in any subject by 28 days following vaccination. Vaccine strain virus was not detected in the throat of any subject.

13 NONCLINICAL PHARMACOLOGY

13.1 Carcinogenesis, Mutagenesis, Impairment of Fertility

Adenovirus Type 4 and Type 7 Vaccine, Live, Oral has not been evaluated for carcinogenic or mutagenic potential, or for impairment of male fertility.

14 CLINICAL STUDIES

14.1 Multicenter Safety and Efficacy Trial

A multicenter, double-blind, randomized, placebo-controlled study in US military recruits evaluated the safety and efficacy of Adenovirus Type 4 and Type 7 Vaccine, Live, Oral to prevent wild Type 4 adenovirus-associated febrile acute respiratory disease (ARD) and to induce neutralizing antibody to Type 7 adenovirus. A seroconversion endpoint rather than prevention of clinical disease was used to assess efficacy of the Type 7 adenovirus vaccine component of this product as the incidence of febrile ARD due to Type 7 adenovirus was not anticipated to be high enough to permit a meaningful statistical assessment of the clinical effect of this vaccine component. Subjects were randomized to either the vaccine group or the placebo group in a 3:1 ratio. 4041 subjects were randomized, and 4040 subjects were analyzed. Females and males aged 17 or older and in good physical health were included in the study. No subjects were immunosuppressed or being treated with systemic immunosuppressive therapy. Baseline serology data is presented in Table 3.

Table 3: Baseline Serology in Multicenter Safety and Efficacy Trial
 | Vaccine; N=3031 | Placebo; N=1009 | Total; N=4040
Type 4 Titer | n (%) | n (%) | n (%)
Negative* | 1906 (63%) | 678 (67%) | 2584 (64%)
Positive** | 1123 (37%) | 331 (33%) | 1454 (36%)
Type 7 Titer
Negative* | 1159 (38%) | 377 (37%) | 1536 (38%)
Positive** | 1870 (62%) | 632 (63%) | 2502 (62%)
* Titer value was <1:4 at visit 0.
** Titer value was ≥1:4 at visit 0.

Adenovirus Type 4 Efficacy and Immunogenicity

Febrile Acute Respiratory Disease (ARD): The results for the primary analysis of vaccine efficacy (VE) for adenovirus Type 4 and rate of wild Type 4 febrile ARD, are summarized in Table 4. Cases were defined as subjects with one or more clinical signs and symptoms of ARD (mild to severe: sore throat, cough, rhinorrhea, nasal congestion, rales or rhonchi), an oral temperature > 100.5°F, and throat culture positive for wild Type 4 adenovirus infection. Vaccine type Adenovirus was distinguished from wild type by a Polymerase Chain Reaction (PCR) assay.

Table 4: Wild Adenovirus Type 4 Febrile ARD Cases (Day 0-56) In the Multicenter Safety and Efficacy Trial
Adeno Type 4 ARD case | Statistic | Vaccine; N=3031 | Placebo; N=1009
Yes | n | 1* | 48
 | VE (95% CI)§ | 99.3% (96.0%, 99.9%)
*one additional subject met the case definition but had non-vaccine serotype (B3) adenovirus
§Vaccine efficacy (VE) defined as: VE = 1 - RR, where RR = P(vaccine)/P(placebo) was the relative risk of ARD attack in subjects who received vaccine compared to placebo; 2-sided confidence interval, by using exact statistical methods.

Seroconversion Rate: Adenovirus Type 4 seroconversion rate is presented in Table 5. Seroconversion is defined as the development of a Type 4 neutralizing antibody titer of greater or equal to 1:8 at Day 26 after vaccination in subjects whose baseline titer was less than 1:4.

Table 5: Adenovirus Type 4 Seroconversion Rate (Day 26) in the Multicenter Safety and Efficacy Study
Adenovirus Type 4 and Type 7 Vaccine, Live Oral |  |  | Placebo
N | Seroconversion |  | N | Seroconversion
 | n | %; (95% CI) |  | n | %; (95% CI)
1841 | 1739 | 94.5%; (93.4%, 95.5%) | 653 | 69 | 10.6 %; (8.2%, 12.9%)

Adenovirus Type 7 Immunogenicity

Febrile Acute Respiratory Disease: No Type 7 adenovirus-associated febrile or afebrile ARD cases were reported for either placebo or vaccine groups. This was expected given the estimated attack rate of adenovirus Type 7 in the military base training setting at the time of the study. Seroconversion was the primary evaluation of Type 7 effectiveness.

Seroconversion Rate: Results for the primary analysis of adenovirus Type 7 efficacy, seroconversion rate at Day 26, are summarized in Table 6. Seroconversion is defined as the development of a Type 7 neutralizing antibody titer of greater or equal to 1:8 at Day 26 after vaccination in subjects whose baseline titer was less than 1:4.

Table 6: Adenovirus Type 7 Seroconversion Rate (Day 26)
Adenovirus Type 4 and Type 7 Vaccine, Live Oral |  |  | Placebo
N | Seroconversion |  | N | Seroconversion
 | n | %; (95% CI) |  | n | %; (95% CI)
1120 | 1051 | 93.8%; (92.4%, 95.2%) | 359 | 19 | 5.3%; (3.0%, 7.6%)

15 REFERENCES

1. Van den Veyver et al. 1998. Detection of intrauterine viral infection using the polymerase chain reaction. Mol Genet Metab, 63: 85-95
2. Calvin et al. 2000. Fatal intrauterine adenoviral endomyocarditis with aortic and pulmonary valve stenosis: diagnosis by polymerase chain reaction. Hum Pathol. 31(11):1433-5
3. Ranucci-Weiss et al. 1998. Intrauterine adenoviral infection associated with fetal non-immune hydrops. Prenat. Diagn. 18(2):182-5
4. Baschat et al., 2003. Is adenovirus a fetal pathogen? Am J Obstet Gynecol. 189(3):758-63.
5. Fields Virology, Fifth Edition, 2007, p2409

16 HOW SUPPLIED/STORAGE AND HANDLING

Adenovirus Type 4 and Type 7 Vaccine, Live, Oral Enteric Coated Tablets is packaged in a carton of two bottles of 100 tablets of each component of the vaccine:

- Adenovirus Type 4 Component of Adenovirus Type 4 and Type 7 Vaccine, Live, Oral enteric coated tablet, a white to off-white, round, coated tablet with stylized b and a 4 imprinted on one side, for oral administration NDC 51285-174-02

- Adenovirus Type 7 Component of Adenovirus Type 4 and Type 7 Vaccine, Live, Oral enteric coated tablet, a light peach, round, coated tablet with stylized b and a 7 imprinted on one side, for oral administration NDC 51285-175-02

- Supplied as a single carton containing 1 x 100 tablets Adenovirus Type 4 Component and 1 x 100 tablets Adenovirus Type 7 Component NDC 51285-138-50

Store refrigerated between 2° and 8° C (35° and 46° F). Do not freeze. Keep bottle tightly closed and protect from moisture. Do not remove desiccant canister from bottle.

17 PATIENT COUNSELING INFORMATION

Adenovirus Type 4 and Type 7 Vaccine, Live, Oral is contraindicated for use in pregnant women.

Inform women to avoid becoming pregnant following vaccination for at least 6 weeks after vaccination to prevent the fetus from being exposed to adenovirus.

Instruct patients to swallow each tablet whole without chewing.

Adenovirus Type 4 and Type 7 Vaccine, Live, Oral contains live virus that is shed in the stool for up to 28 days following vaccination and can cause disease if transmitted. It is given to individuals, undergoing intensive military training, who have limited contact with pregnant women, children under age seven and persons with compromised immune systems. To minimize the risk for transmitting and infecting others with the virus, instruct patients to take the following precautions during the 28-day period following vaccination:

- Observe proper personal hygiene, such as, frequent hand washing, especially following bowel movements.
- Caution is advised when in close contact with children less than 7 years of age, immunocompromised individuals (e.g., HIV infected, has cancer, or is receiving cancer treatments) and pregnant women because they may be more vulnerable to infection if exposed to the virus.

If anyone has any questions or concerns regarding this vaccine, they should speak with their healthcare provider.

Manufactured by:
Teva Women's Health, Inc.
West Chester, PA 19380

Manufactured for:
Teva Pharmaceuticals
Parsippany, NJ 07054

©2022 Teva Pharmaceuticals

Rev. 7/2022

Package/Label Display Panel, Type 4 Component

Adenovirus Type 4 Component of Adenovirus Type 4 and Type 7 Vaccine, Live, Oral Tablets 100s Label Text

NDC 51285-174-02

Rx only

Adenovirus Type 4 Component

Of Adenovirus Type 4 and

Type 7 Vaccine, Live, Oral

Enteric coated tablets,

For oral administration

NOT TO BE USED ALONE

Take with Adenovirus Type 7 Component

100 tablets

teva

Package/Label Display Panel, Type 7 Component

Adenovirus Type 7 Component of Adenovirus Type 4 and Type 7 Vaccine, Live, Oral Tablets 100s Label Text

NDC 51285-175-02

Rx only

Adenovirus Type 7 Component

Of Adenovirus Type 4 and

Type 7 Vaccine, Live, Oral

Enteric coated tablets,

For oral administration

NOT TO BE USED ALONE

Take with Adenovirus Type 4 Component

100 tablets

teva

Package/Label Display Panel, Adenovirus Type 4 and Type 7 Vaccine, Live, Oral Kit Carton, Part 2 of 2

Adenovirus Type 4 and Type 7 Vaccine, Live, Oral Tablets Kit Carton Text

NDC 51285-138-50

Adenovirus Type 4 and Type 7

Vaccine, Live, Oral

Enteric Coated Tablets for Oral Administration

- 4 7

This vaccine product contains two (2) components.

Package contains:

One bottle of 100 tablets of Adenovirus Type 4 Component and

One bottle of 100 tablets of Adenovirus Type 7 Component

One tablet of Adenovirus Type 4 Component and

one tablet of Adenovirus Type 7 Component are to

be taken at the same time.

Rx only

teva